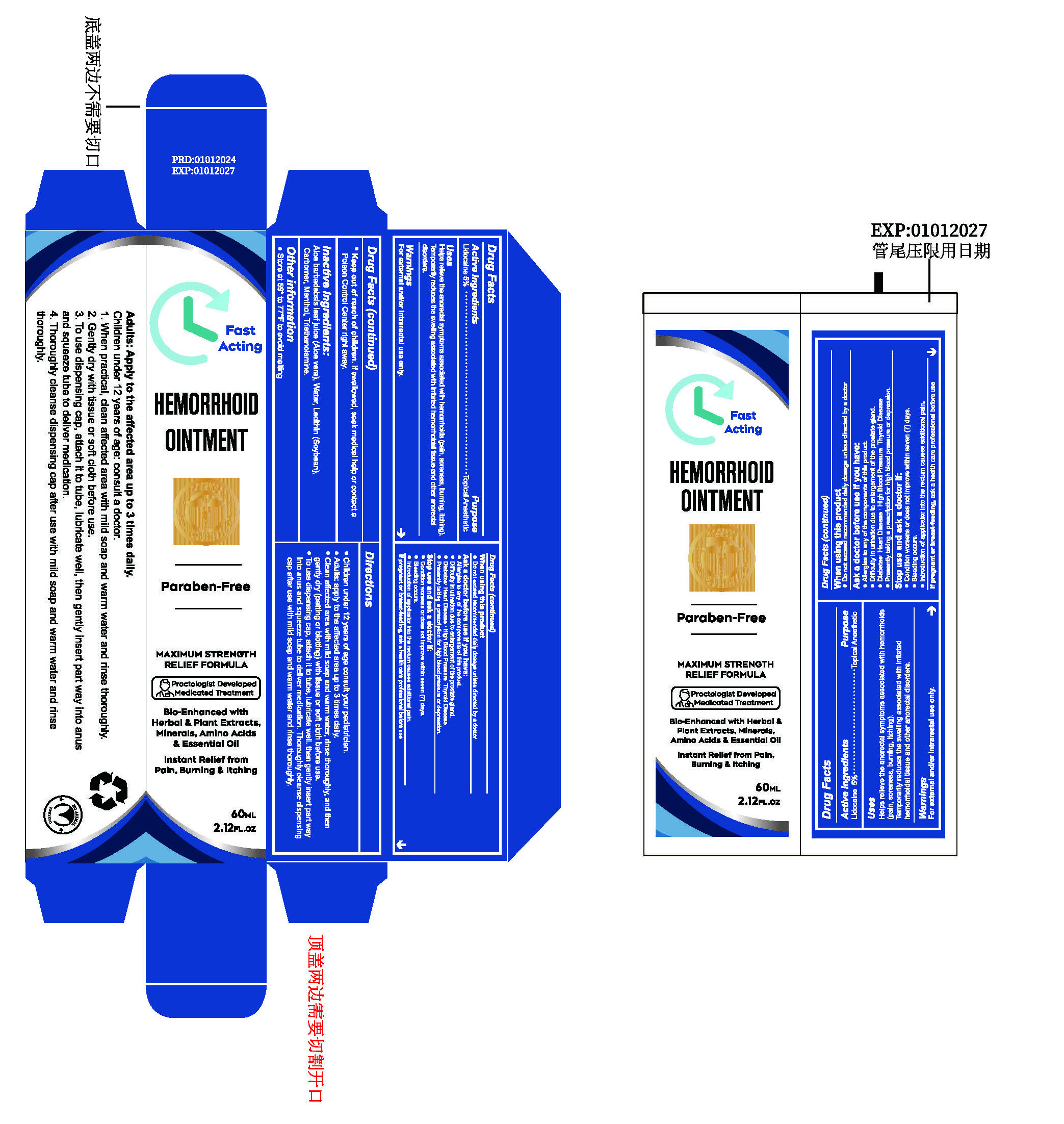 DRUG LABEL: HEMORRHOID OINTMENTS
NDC: 84023-401 | Form: PASTE
Manufacturer: Shenzhen Yangan Technology Co., Ltd.
Category: otc | Type: HUMAN OTC DRUG LABEL
Date: 20240130

ACTIVE INGREDIENTS: LIDOCAINE 5 g/100 mL
INACTIVE INGREDIENTS: LECITHIN, SOYBEAN; TROLAMINE; WATER; CARBOMER HOMOPOLYMER, UNSPECIFIED TYPE; MENTHOL; ALOE

Hemorrhoid Ointment

Hemorrhoid Ointment

ACTIVE INGREDIENT

Lidocaine 5%

PURPOSE

Topical Anesthetic

INDICATIONS AND USAGE

Helps relieve the anorectal symptoms associated with hemorrhoids (pain, soreness, burnina, itching).
Temporarily reduces the sweling associated with irritated hemorrhoidal tissue and other anorectal disorders.

WARNINGS

For externaand/or intrarectal use only

WHEN USING

Do not exceed recommended daily dosage unless directed by a doctor.

Ask a doctor before use if you have:
Allergies to any of the components of this product.
Difficulty in urination due to enlargement of the prostate gland.
Diabetes: Heart Disease : High Blood Pressure Thyroid Disease.
Presently taking a prescription for high blood pressure or depression.

STOP USE

Condition worsens or does not improve within seven (7) days.
Bleeding occurs.
Introduction of applicator into the rectum causes additional pain.

DO NOT USE

lf pregnant or breast-feeding, ask a health care professional before use

Keep out of reach of children. lf swallowed, seek medical help or contact a Poison Contro Center right away.

DOSAGE AND ADMINISTRATION

Children under 12 years of age consult your pediatrician.
Adults: apply to the affected area up to 3 times daily.
Clean affected area with mild soap and warm water, rinse thoroughly, and then gently dry (patting or blotting) with tissue or soft cloth before use.
To use dispensing cap, attach it to tube, lubricate well. then gently insert part way into anus and squeeze tube to deliver medication. Thoroughly cleanse dispensing cap after use with mild soap and warm water and rinse thoroughly.

STORAGE AND HANDLING

Store at 59* to 77*F to avoid melting

INACTIVE INGREDIENT

Aloe barbadebsis leaf juice (Aloe vera)
Water
Lecithin (Soybean)

Carbomer
Menthol
Triethanolamine